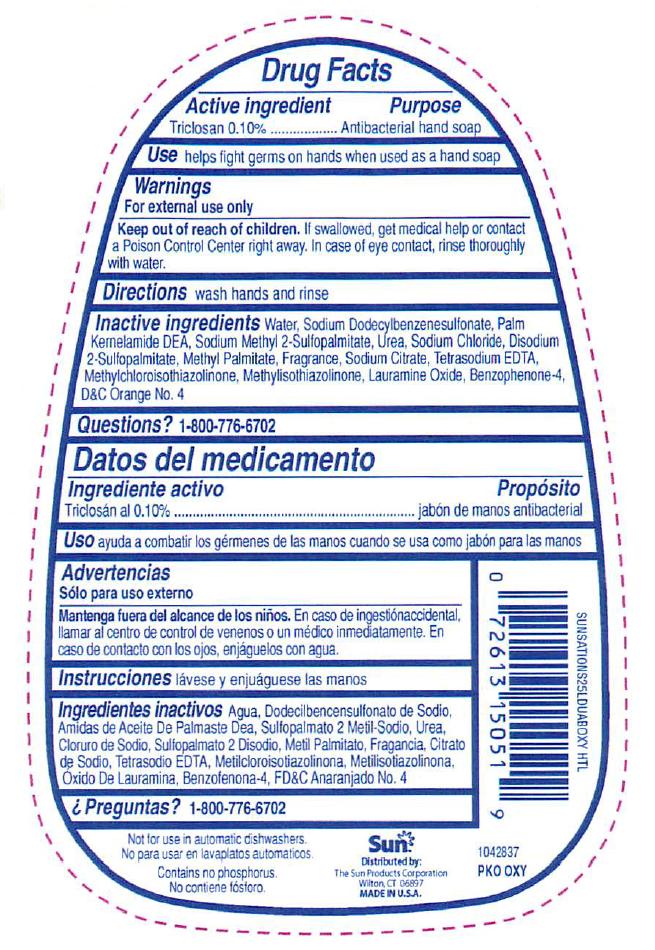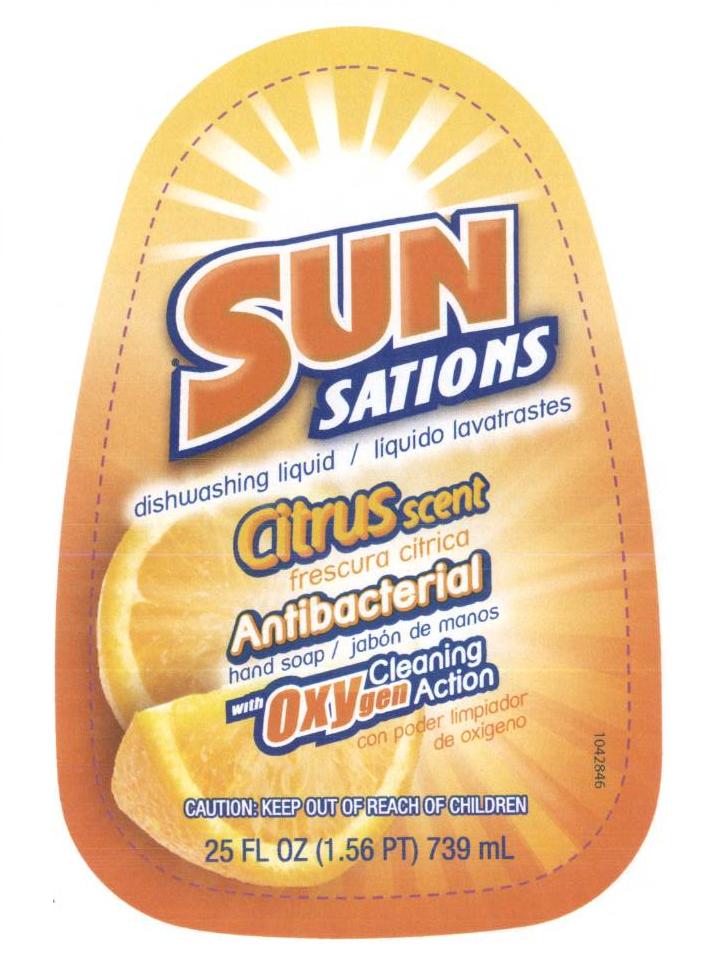 DRUG LABEL: Antibacterial
NDC: 63691-002 | Form: SOAP
Manufacturer: Sun Products Corporation
Category: otc | Type: HUMAN OTC DRUG LABEL
Date: 20111230

ACTIVE INGREDIENTS: Triclosan .1 mL/100 mL
INACTIVE INGREDIENTS: Water

Drug Facts

Drug Facts

Active ingredient

Triclosan 0.10% (or % in formula)

INDICATIONS AND USAGE

Use helps fight germs on hands when used as a hand soap

Warnings

For external use only

Keep out of reach of children. If swallowed, get medical help or contact a Poison Control Center right away. In case of eye contact, rinse thoroughly with water.

Purpose

Antibacterial hand soap

Questions? (insert proper phone number)

DOSAGE AND ADMINISTRATION

Directions wash hands and rinse

Inactive ingredients water, .....

PACKAGE LABEL

Enter section text here

Place holder text

Antibac1

label_back.jpg

Antibac2

label_front.jpg